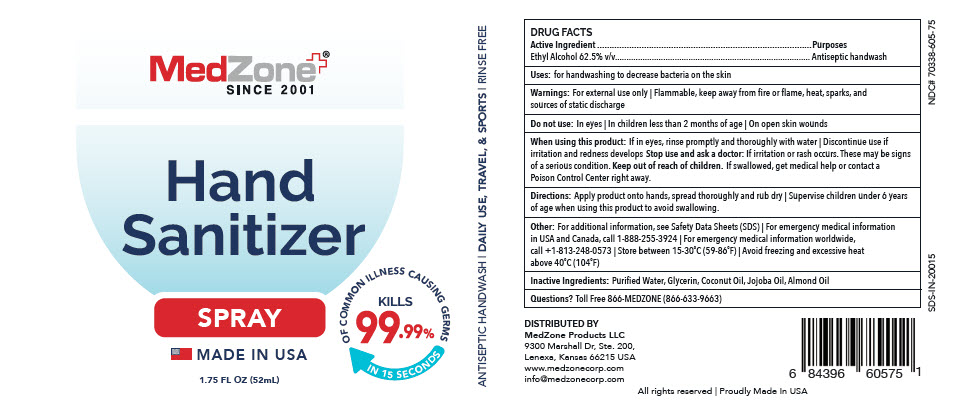 DRUG LABEL: Hand Sanitizer
NDC: 70338-605 | Form: SPRAY
Manufacturer: MedZone Products, LLC
Category: otc | Type: HUMAN OTC DRUG LABEL
Date: 20200326

ACTIVE INGREDIENTS: Alcohol 0.625 mL/1 mL
INACTIVE INGREDIENTS: Water; Glycerin; Coconut Oil; Jojoba Oil; Almond Oil

Hand Sanitizer

DRUG FACTS

Active Ingredient

Ethyl Alcohol 62.5% v/v

Purposes

Antiseptic handwash

Uses

for handwashing to decrease bacteria on the skin

Warnings

For external use only | Flammable, keep away from fire or flame, heat, sparks, and sources of static discharge

Do not use

In eyes | In children less than 2 months of age | On open skin wounds

When using this product

If in eyes, rinse promptly and thoroughly with water | Discontinue use if irritation and redness develops

Stop use and ask a doctor

If irritation or rash occurs. These may be signs of a serious condition.

Keep out of reach of children. If swallowed, get medical help or contact a Poison Control Center right away.

Directions

Apply product onto hands, spread thoroughly and rub dry | Supervise children under 6 years of age when using this product to avoid swallowing.

Other

For additional information, see Safety Data Sheets (SDS) | For emergency medical information in USA and Canada, call 1-888-255-3924 | For emergency medical information worldwide, call +1-813-248-0573 | Store between 15-30°C (59-86°F) | Avoid freezing and excessive heat above 40°C (104°F)

Inactive Ingredients

Purified Water, Glycerin, Coconut Oil, Jojoba Oil, Almond Oil

Questions?

Toll Free 866-MEDZONE (866-633-9663)

DISTRIBUTED BY
MedZone Products LLC
9300 Marshall Dr, Ste. 200,
Lenexa, Kansas 66215

PRINCIPAL DISPLAY PANEL - 52 mL Bottle Label

MedZone®
SINCE 2001

Hand
Sanitizer

SPRAY

MADE IN USA

KILLS
99.99%
OF COMMON ILLNESS CAUSING GERMS
IN 15 SECONDS

1.75 FL OZ (52mL)